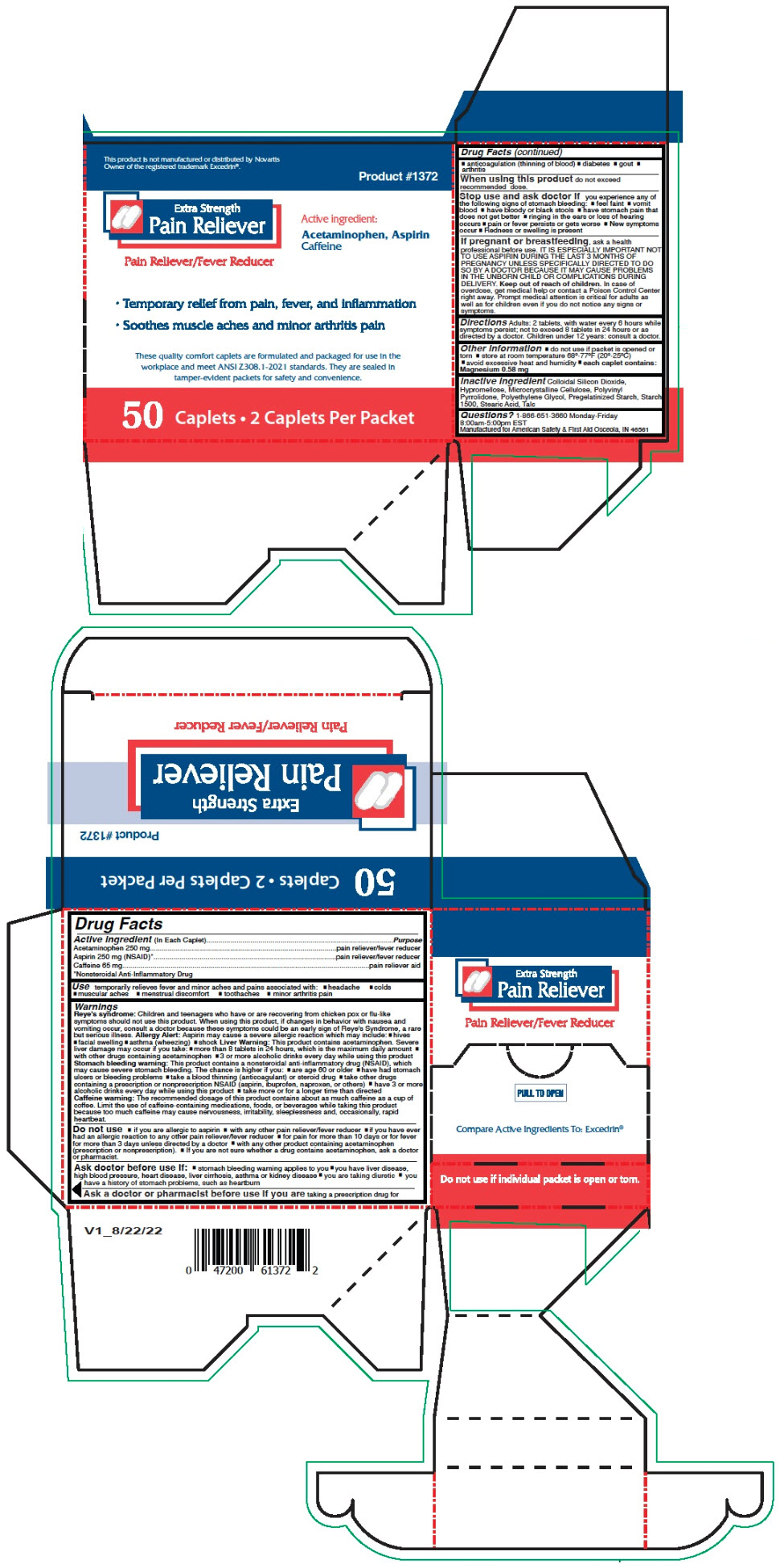 DRUG LABEL: Extra Strength Pain Reliever
NDC: 73598-1372 | Form: CAPSULE, COATED
Manufacturer: JHK Inc dba American Safety & First Aid
Category: otc | Type: HUMAN OTC DRUG LABEL
Date: 20240425

ACTIVE INGREDIENTS: ACETAMINOPHEN 250 mg/1 1; ASPIRIN 250 mg/1 1; CAFFEINE 65 mg/1 1
INACTIVE INGREDIENTS: SILICON DIOXIDE; HYPROMELLOSE, UNSPECIFIED; MICROCRYSTALLINE CELLULOSE; POLYETHYLENE GLYCOL, UNSPECIFIED; STARCH, CORN; STEARIC ACID; TALC

Extra Strength Pain Reliever

Drug Facts

ACTIVE INGREDIENT

Active ingredient (In Each Caplets) | Purpose
Acetaminophen 250 mg | pain reliever/fever reducer
Aspirin 250 mg (NSAID) [Nonsteroidal Anti-Inflammatory Drug] | pain reliever/fever reducer
Caffeine 65 mg | pain reliever aid

Use

temporarily relieves fever and minor aches and pains associated with:

- headache
- colds
- muscular aches
- menstrual discomfort
- toothaches
- minor arthritis pain

Warnings

Reye's syndrome

Children and teenagers who have or are recovering from chicken pox or flu-like symptoms should not use this product. When using this product, if changes in behavior with nausea and vomiting occur, consult a doctor because these symptoms could be an early sign of Reye's Syndrome, a rare but serious illness.

Allergy Alert

Aspirin may cause a severe allergic reaction which may include:

- hives
- facial swelling
- asthma (wheezing)
- shock

Liver Warning

This product contains acetaminophen. Severe liver damage may occur if you take:

- more than 8 tablets in 24 hours, which is the maximum daily amount
- with other drugs containing acetaminophen
- 3 or more alcoholic drinks every day while using this product

Stomach bleeding warning

This product contains a nonsteroidal anti-inflammatory drug (NSAID), which may cause severe stomach bleeding. The chance is higher if you:

- are age 60 or older
- have had stomach ulcers or bleeding problems
- take a blood thinning (anticoagulant) or steroid drug
- take other drugs containing a prescription or nonprescription NSAID (aspirin, ibuprofen, naproxen, or others)
- have 3 or more alcoholic drinks every day while using this product
- take more or for a longer time than directed

Caffeine warning

The recommended dosage of this product contains about as much caffeine as a cup of coffee. Limit the use of caffeine-containing medications, foods, or beverages while taking this product because too much caffeine may cause nervousness, irritability, sleeplessness and, occasionally, rapid heartbeat.

Do not use

- if you are allergic to aspirin
- with any other pain reliever/fever reducer
- if you have ever had an allergic reaction to any other pain reliever/fever reducer
- for pain for more than 10 days or for fever for more than 3 days unless directed by a doctor
- with any other product containing acetaminophen (prescription or nonprescription).
- If you are not sure whether a drug contains acetaminophen, ask a doctor or pharmacist.

Ask doctor before use if

- stomach bleeding warning applies to you
- you have liver disease, high blood pressure, heart disease, liver cirrhosis, asthma or kidney disease
- you are taking diuretic
- you have a history of stomach problems, such as heartburn

Ask a doctor or pharmacist before use if you are taking a prescription drug for

- anticoagulation (thinning of blood)
- diabetes
- gout
- arthritis

When using this product do not exceed recommended dose.

Stop use and ask doctor if you experience any of the following signs of stomach bleeding:

- feel faint
- vomit blood
- have bloody or black stools
- have stomach pain that does not get better
- ringing in the ears or loss of hearing occurs
- pain or fever persists or gets worse
- New symptoms occur
- Redness or swelling is present

PREGNANCY OR BREAST FEEDING

If pregnant or breastfeeding, ask a health professional before use. IT IS ESPECIALLY IMPORTANT NOT TO USE ASPIRIN DURING THE LAST 3 MONTHS OF PREGNANCY UNLESS SPECIFICALLY DIRECTED TO DO SO BY A DOCTOR BECAUSE IT MAY CAUSE PROBLEMS IN THE UNBORN CHILD OR COMPLICATIONS DURING DELIVERY.

Keep out of reach of children. In case of overdose, get medical help or contact a Poison Control Center right away. Prompt medical attention is critical for adults as well as for children even if you do not notice any signs or symptoms.

Directions Adults

2 tablets, with water every 6 hours while symptoms persist; not to exceed 8 tablets in 24 hours or as directed by a doctor. Children under 12 years: consult a doctor.

Other Information

- do not use if packet is opened or torn
- store at room temperature 68º-77ºF (20º-25ºC)
- avoid excessive heat and humidity
- each caplet contains: Magnesium 0.58 mg

Inactive ingredient

Colloidal Silicon Dioxide, Hypromellose, Microcrystalline Cellulose, Polyvinyl Pyrrolidone, Polyethylene Glycol, Pregelatinized Starch, Starch 1500, Stearic Acid, Talc

Questions?

1-866-651-3660 Monday-Friday

8:00am-5:00pm EST

Manufactured for American Safety & First Aid Osceola, IN 46561

PRINCIPAL DISPLAY PANEL - 50 Caplet Packet Box

This product is not manufactured or distributed by Novartis
Owner of the registered trademark Excedrin®.

Product #1372

Extra Strength
Pain Reliever

Pain Reliever/Fever Reducer

Active ingredient:
Acetaminophen, Aspirin
Caffeine

- Temporary relief from pain, fever, and inflammation
- Soothes muscle aches and minor arthritis pain

These quality comfort caplets are formulated and packaged for use in the
workplace and meet ANSI Z308. 1-2021 standards. They are sealed in
tamper-evident packets for safety and convenience.

50 Caplets • 2 Caplets Per Packet